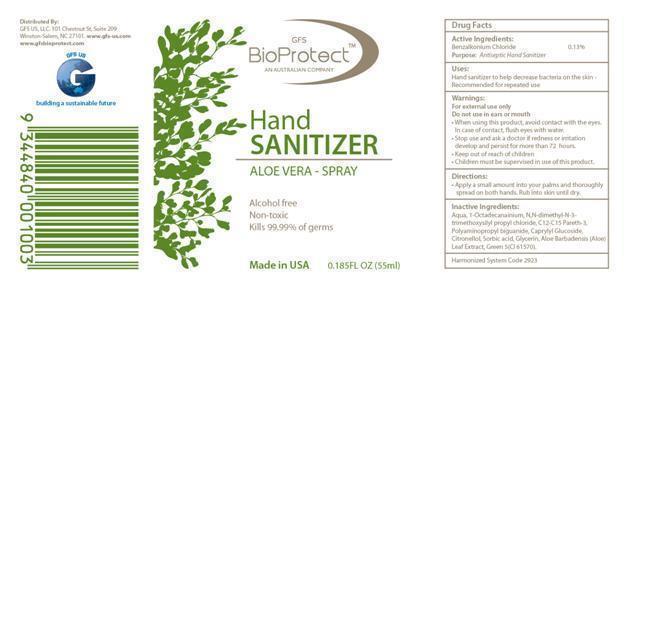 DRUG LABEL: GFS BIOPROTECT HAND SANITIZER ALOE VERA
NDC: 76426-011 | Form: SPRAY
Manufacturer: GFS US LLC
Category: otc | Type: HUMAN OTC DRUG LABEL
Date: 20130403

ACTIVE INGREDIENTS: Benzalkonium Chloride 0.0013 g/1 g
INACTIVE INGREDIENTS: Water; DIMETHYLOCTADECYL(3-(TRIMETHOXYSILYL)PROPYL)AMMONIUM CHLORIDE; C12-15 PARETH-12; POLYAMINOPROPYL BIGUANIDE; CAPRYLYL GLUCOSIDE; .BETA.-CITRONELLOL, (+/-)-; SORBIC ACID; GLYCERIN; ALOE VERA LEAF; D&C Green No. 5

DRUG FACTS

DESCRIPTION

BioProtect Hand Sanitizer contains 0.13% antiseptic agent Benzalkonium Chloride formulated with Water,1-Ocatadecanaminium, N-N-dimethyl-N-[3-(trimethoxysilyl)propyl]-,chloride, C12-C15 Pareth-3, Polyaminopropyl biguanide, Caprylyl glucoside, Citronellol, Sorbic Acid, Glycerin, Aloe Barbadensis (Aloe) Leaf Extract, and D and C Green No.5. It is alcohol-free, non-toxic and kills 99.99% of germs.

ACTIVE INGREDIENT

Benzalkonium Chloride 0.13%.............................................Antiseptic

PURPOSE

- Antispetic

INDICATIONS AND USAGE

- Hand sanitizer to help decrease bacteria on skin

- Recommended for repeated use

WARNINGS

- For external use only

- Do not use in ears or mouth

- Keep out of reach on children

- Children must be supervised in use of this product

DOSAGE AND ADMINISTRATION

- Apply a small amount into your palm and thoroughly spread on both hands
- Rub into skin until dry

GENERAL PRECAUTIONS

- Review MSDS before handling the product

- When using this product do not use in ears or mouth

- Avoid contact with eyes
- In case of eye contact, rinse eyes thoroughly with water

- Stop use and ask a doctor if skin irritation or redness develops and persists for more than 72 hours

INACTIVE INGREDIENT

- Water,1-Ocatadecanaminium, N-N-dimethyl-N-[3-(trimethoxysilyl)propyl]-,chloride, C12-C15 Pareth-3, Polyaminopropyl biguanide, Caprylyl glucoside, Citronellol, Sorbic Acid, Glycerin, Aloe Barbadensis (Aloe) Leaf Extract, and D and C Green No.5